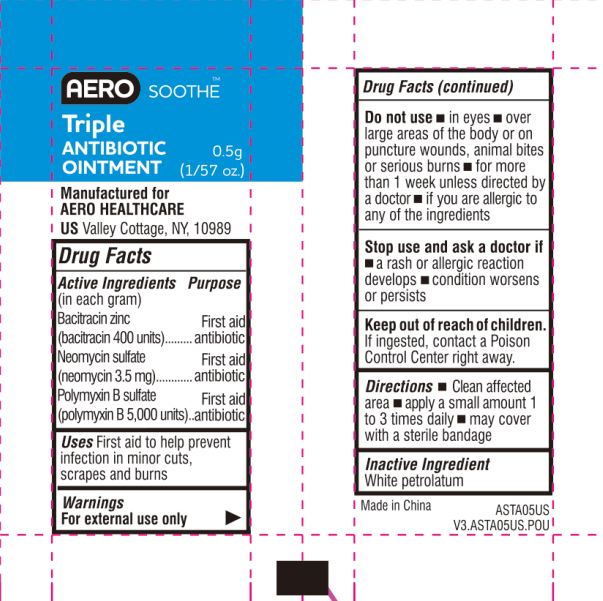 DRUG LABEL: Aerosoothe
NDC: 55305-123 | Form: OINTMENT
Manufacturer: Aero Healthcare US LLC
Category: otc | Type: HUMAN OTC DRUG LABEL
Date: 20250829

ACTIVE INGREDIENTS: BACITRACIN ZINC 400 [iU]/1 g; NEOMYCIN SULFATE 5 mg/1 g; POLYMYXIN B SULFATE 5000 [iU]/1 g
INACTIVE INGREDIENTS: PETROLATUM

AEROSOOTHE TRIPLE ANTIBIOTIC OINTMENT

ACTIVE INGREDIENT

Active Ingredients: In each gram-Neomycin Sulfate-5 mg (equivalent to 3.5 mg Neomycin), Polymixin B Sulfate-5000 I.U., Bacitracin Zinc-400 I.U.

Purpose

First Aid Antibiotic

Warnings:

For external use only.

Do not use:

- in eyes
- over large areas of the body or on puncture wounds, animal bites or serious burns
- for more than 1 week unless directed by a doctor
- if you are allergic to any of the ingredients due to anaphylactic shock

KEEP OUT OF REACH OF CHILDREN

IF INGESTED, CONTACT A POISON CONTROL CENTER RIGHT AWAY.

DIRECTIONS

- CLEAN AFFECTED AREA
- APPPLY A SMALL AMOUNT 1 TO 3 TIMES DAILY
- MAY COVER WITH A STERILE BANDAGE

INACTIVE INGREDIENT

INACTIVE INGREDIENT: WHITE PETROLATUM

Indications & Usage

FIRST AID TO HELP PREVENT INFECTION IN MINOR SCRAPES, CUTS AND BURNS.